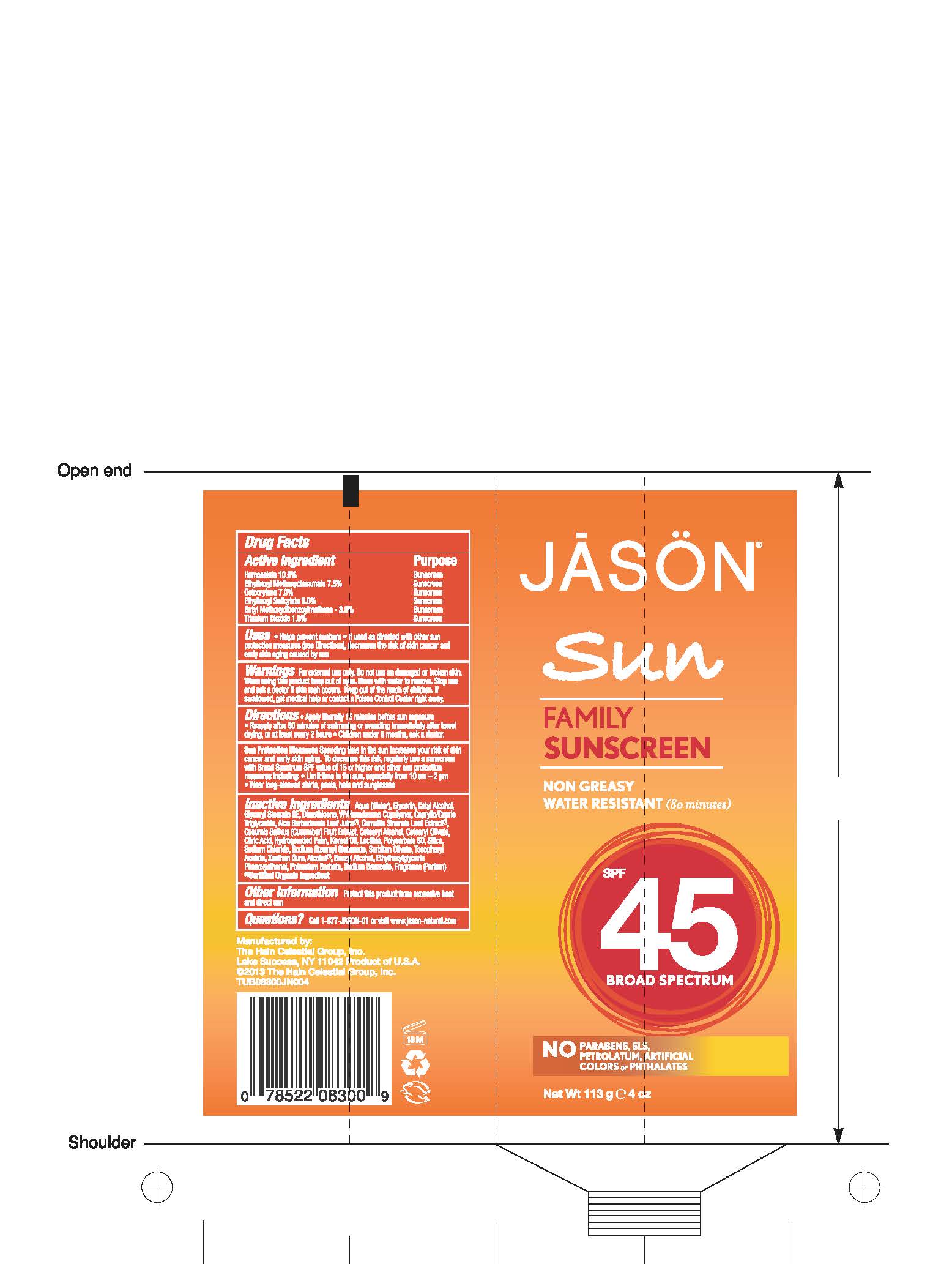 DRUG LABEL: Jason Sun Family Sunscreen Broad Spectrum SPF45
NDC: 61995-0830 | Form: LOTION
Manufacturer: The Hain Celestial Group, Inc.
Category: otc | Type: HUMAN OTC DRUG LABEL
Date: 20150109

ACTIVE INGREDIENTS: HOMOSALATE 10 g/100 g; OCTISALATE 5 g/100 g; OCTOCRYLENE 7 g/100 g; AVOBENZONE 3 g/100 g; OCTINOXATE 7.5 g/100 g; TITANIUM DIOXIDE 1 g/100 g
INACTIVE INGREDIENTS: CITRIC ACID MONOHYDRATE; GREEN TEA LEAF; CUCUMBER; ALOE VERA LEAF; GLYCERIN; WATER; VINYLPYRROLIDONE/HEXADECENE COPOLYMER; SODIUM STEAROYL GLUTAMATE; .ALPHA.-TOCOPHEROL ACETATE; GLYCERYL STEARATE SE; POTASSIUM SORBATE; CETYL ALCOHOL; DIMETHICONE; XANTHAN GUM; CETOSTEARYL ALCOHOL; HYDROGENATED PALM KERNEL OIL; LECITHIN, SOYBEAN; POLYSORBATE 60; MEDIUM-CHAIN TRIGLYCERIDES; CETEARYL OLIVATE; SILICON DIOXIDE; SODIUM CHLORIDE; SORBITAN OLIVATE; SODIUM BENZOATE; ALCOHOL; ETHYLHEXYLGLYCERIN; BENZYL ALCOHOL; PHENOXYETHANOL

Active Ingredient

Homosalate - 10.0%

Octocrylene - 7.0%

Ethyl Methoxycinnamate - 7.5

Ethylhexyl Salicylate - 5.0%

Butyl Methoxydibenzoylmethane - 3.0%

Titanium Dioxide - 1.0%

DOSAGE AND ADMINISTRATION

Apply liberally 15 minutes before sun exposure. Reapply after 80 minutes of swimming or sweating, immediately after towel drying and at least every 2 hours.

PURPOSE

Sunscreen

WARNINGS

For external use only. Do not use on damaged or broken skin. When using this product keep out of eyes. Rinse with water to remove. Stop use and ask a doctor if skin rash occurs.

Keep out of reach of children. If swallowed get medical help or contact Poison Center right away.

INACTIVE INGREDIENT

Water, Glycerin, Glyceryl Stearate SE, Cetyl Alcohol, Dimethicone, Cetearyl Alcohol, VP/Hexadecene Copolymer, Caprylic/Capric Triglyceride, Hydrogenated Palm Cernel Oil, Aloe Barbadensis Leaf Juice(1), Camellia Sinensis Leaf Extract (1),Cucumis Sativus (Cucumber) Fruit Extract, Cetearyl Olivate, Polysorbate 60, Lecithin, Silica, Sodium Chloride, Sodium Stearoyl Glutamate, Sorbitan Olivate, Tocopheryl Acetate, Xanthan Gum, Alcohol (1), Citric Acid, Benzyl Alcohol, Ethylhexylglycerin, Phenoxyethanol, Potassium Sorbate, Sodium Benzoate.

(1) Certified Organic Ingredient

INDICATIONS AND USAGE

Helps prevents sunburns. If used as directed with other sun protection measures, decreases risk of skin cancer and early skin aging caused by sun exposure. Skin Protection Measures: Spending time in the sun increases your risk of skin cancer and early skin aging. To decrease risk, regularly use sunscreen with Broad Spectrum SPF 15 or higher and other protective measures including: limit time in sun, especially from10am to 2pm, and wear long sleeved shirts, pants, hats and sunglases.